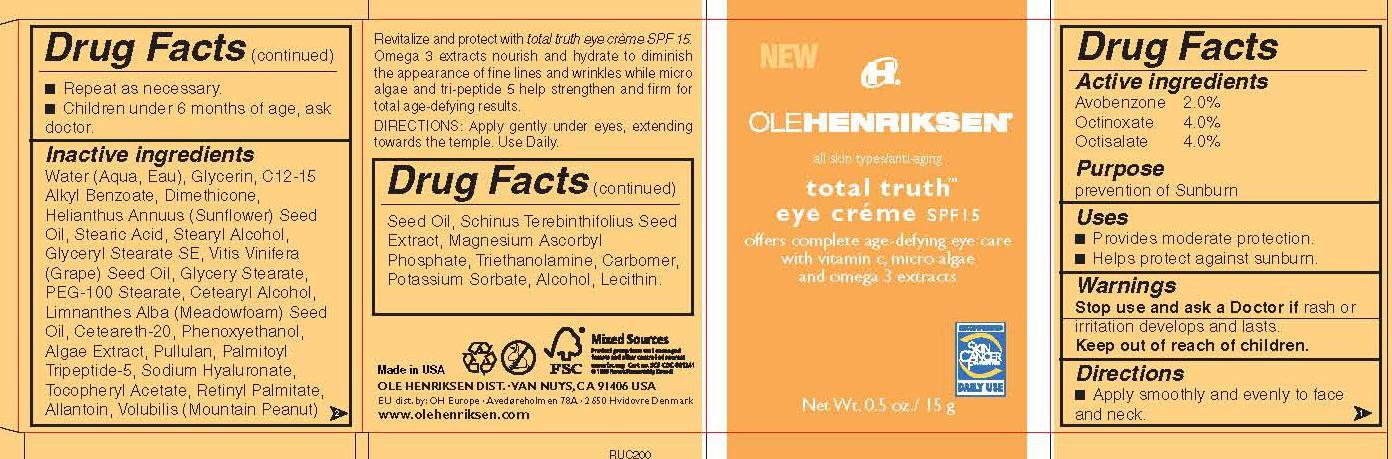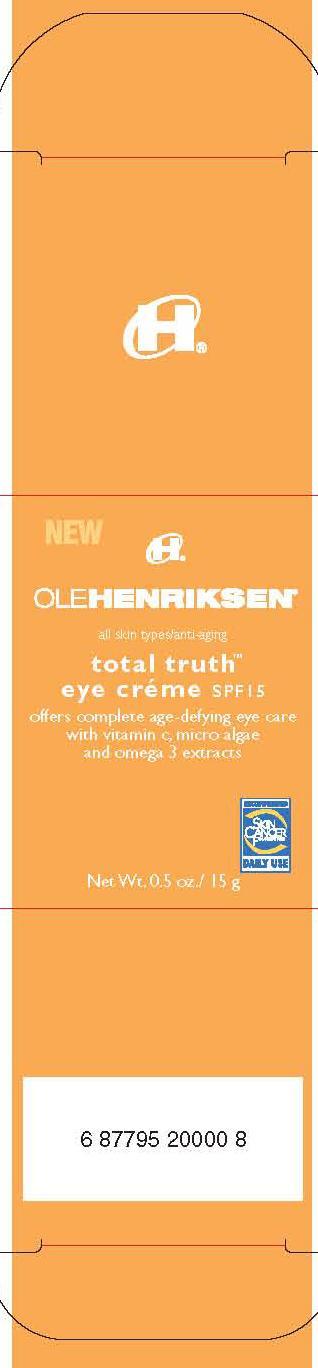 DRUG LABEL: Total Truth Eye Creme SPF 15
NDC: 51770-154 | Form: CREAM
Manufacturer: Ole Henriksen of Denmark
Category: otc | Type: HUMAN OTC DRUG LABEL
Date: 20130708

ACTIVE INGREDIENTS: AVOBENZONE 2 g/100 g; OCTINOXATE 4 g/100 g; OCTISALATE 4 g/100 g
INACTIVE INGREDIENTS: GLYCERIN; ALKYL (C12-15) BENZOATE; DIMETHICONE; SUNFLOWER OIL; STEARIC ACID; STEARYL ALCOHOL; GLYCERYL MONOSTEARATE; PEG-100 STEARATE; CETOSTEARYL ALCOHOL; MEADOWFOAM SEED OIL; POLYOXYL 20 CETOSTEARYL ETHER; PHENOXYETHANOL; PULLULAN; PALMITOYL TRIPEPTIDE-5; HYALURONATE SODIUM; VITAMIN A PALMITATE; ALLANTOIN; BRAZILIAN PEPPER; MAGNESIUM ASCORBYL PHOSPHATE; TROLAMINE; POTASSIUM SORBATE; ALCOHOL

Total Truth Eye Cream SPF 15

Active Ingredients Purpose
Avobenzone 2.0% prevention of sunburn
Octinoxate 4.0% prevention of sunburn
Octisalate 4.0% prevention of sunburn

PURPOSE

prevention of sunburn

keep out of reach of children

INDICATIONS AND USAGE

provides moderate protection

helps against sunburn

stop use and ask a doctor if rash or irritation develops and lasts

DOSAGE AND ADMINISTRATION

apply smoothly and evenly to face and neck
repeat as necessary
children under 6 month of age , ask doctor.

INACTIVE INGREDIENT

Water (Aqua, Eau), Glycerin, C12-15 Alkyl Benzoate, Dimethicone,Helianthus Annuus (Sunflower) Seed Oil, Stearic Acid, Stearyl Alcohol,Glyceryl Stearate SE, Vitis Vinifera(Grape) Seed Oil, Glycery Stearate,PEG-100 Stearate, Cetearyl Alcohol,Limnanthes Alba (Meadowfoam) Seed Oil, Ceteareth-20, Phenoxyethanol,Algae Extract, Pullulan, Palmitoyl Tripeptide-5, Sodium Hyaluronate,Tocopheryl Acetate, Retinyl Palmitate, Allantoin, Volubilis (Mountain Peanut)Seed Oil, Schinus Terebinthifolius Seed Extract, Magnesium Ascorbyl Phosphate, Triethanolamine, Carbomer,Potassium Sorbate, Alcohol, Lecithin.

PACKAGE LABEL

OleHenriksen

total truth

eye creme SPF 15

Net Wt. 0.5oz./ 15g